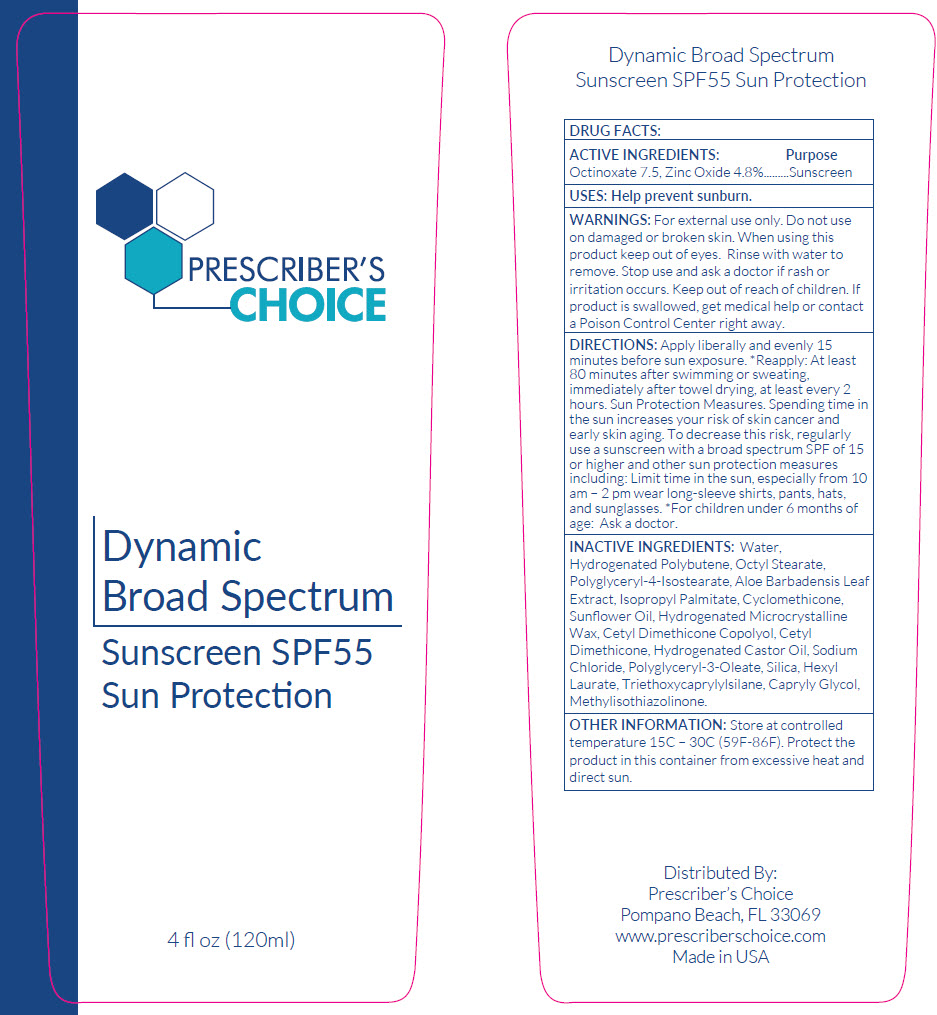 DRUG LABEL: Prescribers Choice  Dynamic Broad Spectrum
NDC: 71876-003 | Form: LOTION
Manufacturer: Prescriber's Choice Inc.
Category: otc | Type: HUMAN OTC DRUG LABEL
Date: 20180921

ACTIVE INGREDIENTS: OCTINOXATE 75 mg/1 mL; ZINC OXIDE 48 mg/1 mL
INACTIVE INGREDIENTS: WATER; OCTYL STEARATE; POLYGLYCERYL-4 ISOSTEARATE; ALOE VERA LEAF; ISOPROPYL PALMITATE; CYCLOMETHICONE; SUNFLOWER OIL; HYDROGENATED CASTOR OIL; SODIUM CHLORIDE; POLYGLYCERYL-3 OLEATE; SILICON DIOXIDE; HEXYL LAURATE; TRIETHOXYCAPRYLYLSILANE; CAPRYLYL GLYCOL; METHYLISOTHIAZOLINONE

Prescriber's Choice Dynamic Broad Spectrum

DRUG FACTS:

ACTIVE INGREDIENTS

Octinoxate 7.5, Zinc Oxide 4.8%

Purpose

Sunscreen

USES

Help prevent sunburn.

WARNINGS

For external use only. Do not use on damaged or broken skin. When using this product keep out of eyes. Rinse with water to remove. Stop use and ask a doctor if rash or irritation occurs.

Keep out of reach of children. If product is swallowed, get medical help or contact a Poison Control Center right away.

DIRECTIONS

Apply liberally and evenly 15 minutes before sun exposure. *Reapply: At least 80 minutes after swimming or sweating, immediately after towel drying, at least every 2 hours. Sun Protection Measures. Spending time in the sun increases your risk of skin cancer and early skin aging. To decrease this risk, regularly use a sunscreen with a broad spectrum SPF of 15 or higher and other sun protection measures including: Limit time in the sun, especially from 10 am – 2 pm wear long-sleeve shirts, pants, hats, and sunglasses. *For children under 6 months of age: Ask a doctor.

INACTIVE INGREDIENTS

Water, Hydrogenated Polybutene, Octyl Stearate, Polyglyceryl-4-Isostearate, Aloe Barbadensis Leaf Extract, Isopropyl Palmitate, Cyclomethicone, Sunflower Oil, Hydrogenated Microcrystalline Wax, Cetyl Dimethicone Copolyol, Cetyl Dimethicone, Hydrogenated Castor Oil, Sodium Chloride, Polyglyceryl-3-Oleate, Silica, Hexyl Laurate, Triethoxycaprylylsilane, Capryly Glycol, Methylisothiazolinone.

OTHER INFORMATION

Store at controlled temperature 15C – 30C (59F-86F). Protect the product in this container from excessive heat and direct sun.

Distributed By:
Prescriber's Choice
Pompano Beach, FL 33069

PRINCIPAL DISPLAY PANEL - 120 ml Bottle Label

PRESCRIBER'S
CHOICE

Dynamic
Broad Spectrum

Sunscreen SPF55
Sun Protection

4 fl oz (120ml)